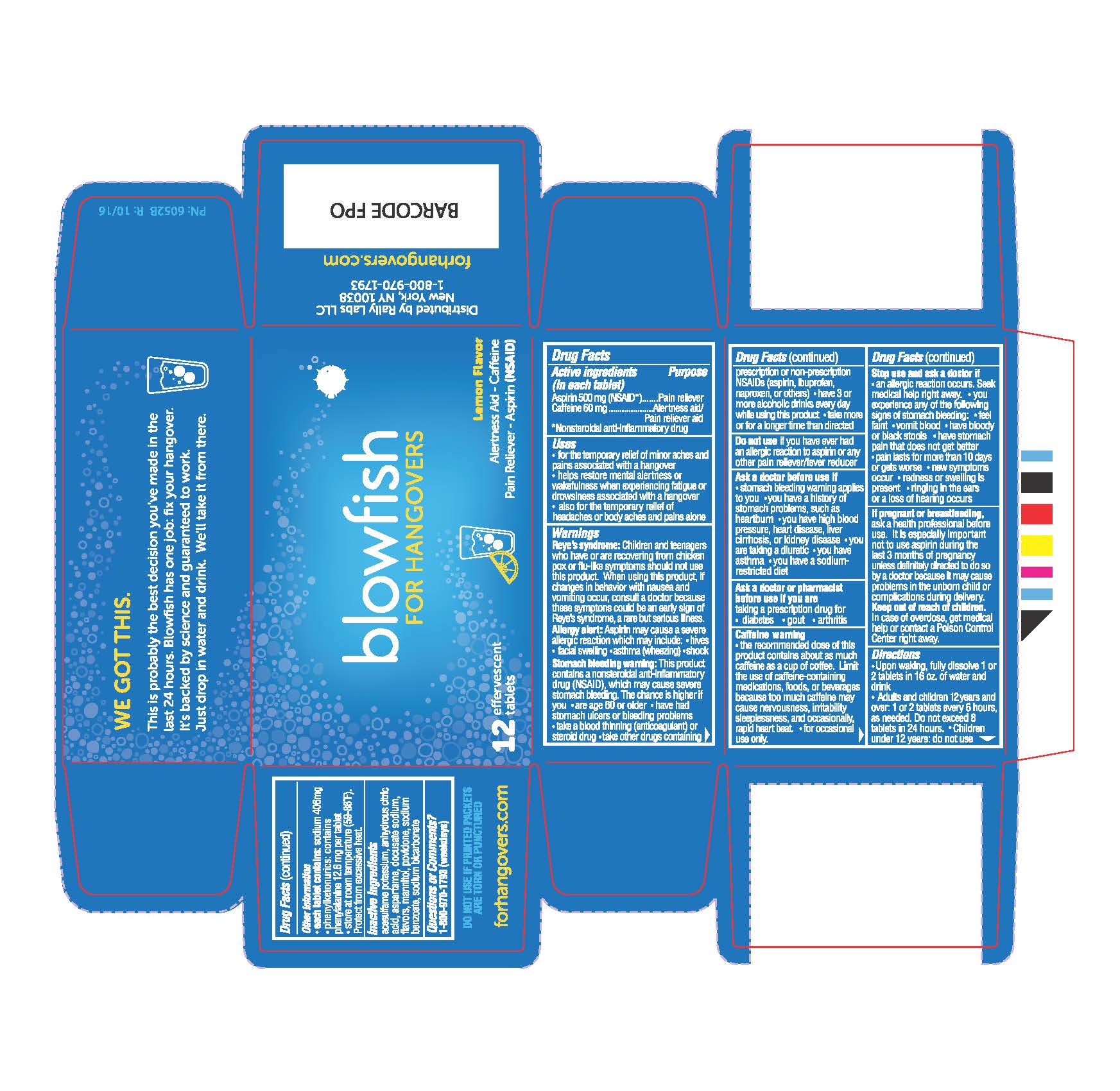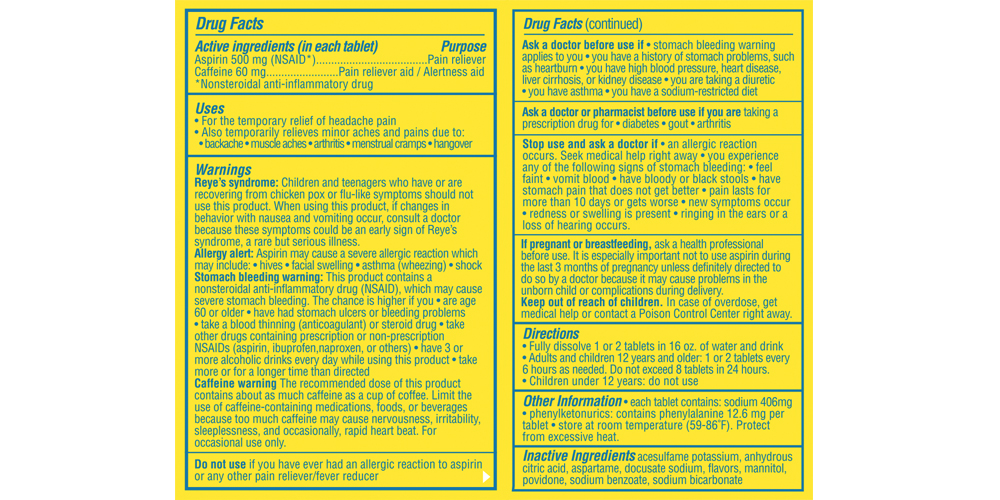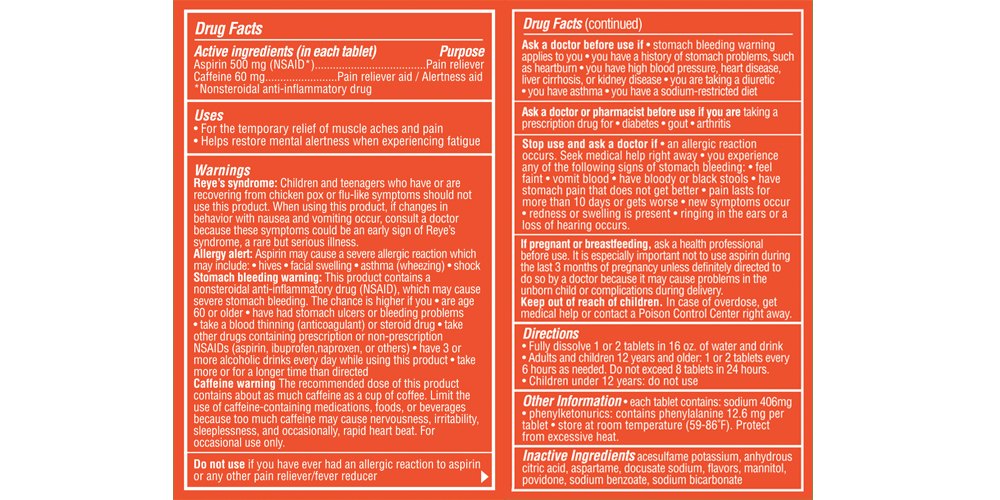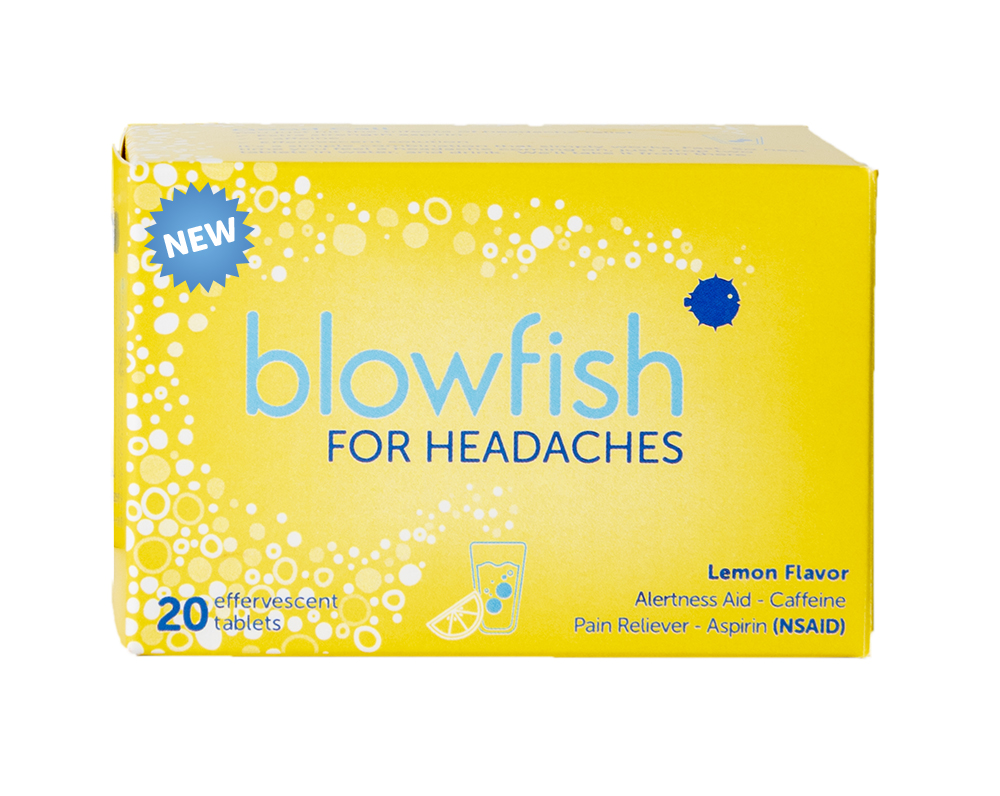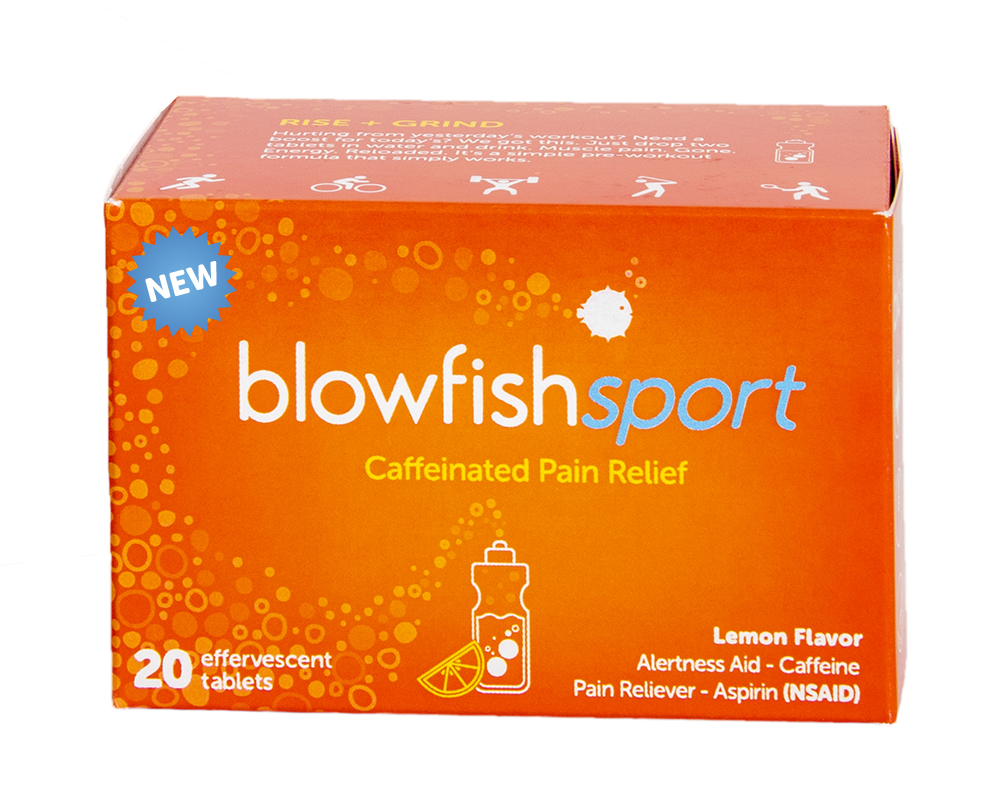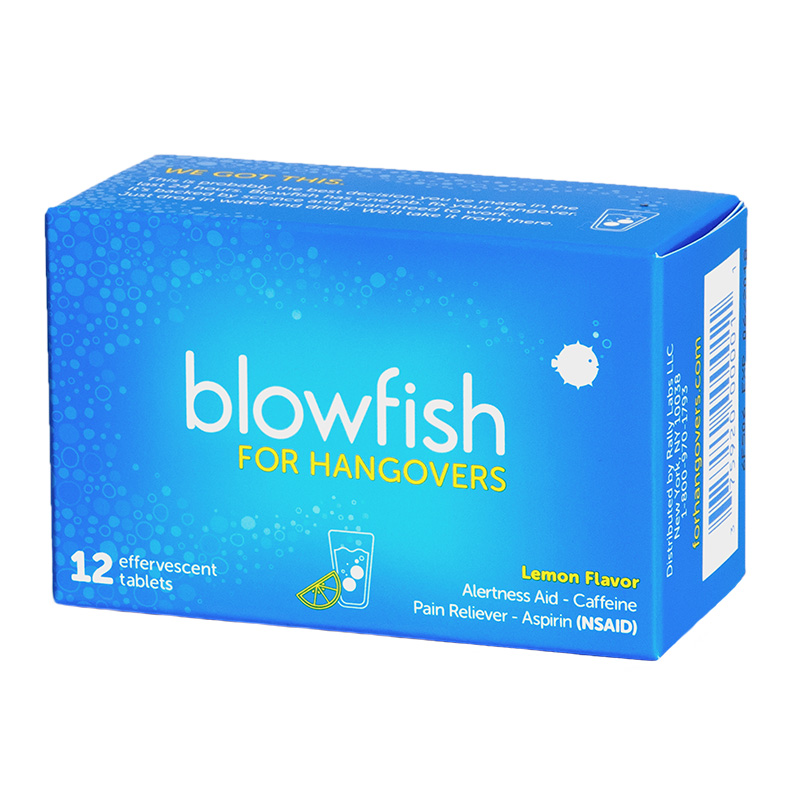 DRUG LABEL: Blowfish
NDC: 75920-0464 | Form: TABLET, EFFERVESCENT
Manufacturer: Rally Labs LLC
Category: otc | Type: HUMAN OTC DRUG LABEL
Date: 20251229

ACTIVE INGREDIENTS: ASPIRIN 500 mg/1 1; CAFFEINE 60 mg/1 1
INACTIVE INGREDIENTS: ACESULFAME POTASSIUM; ANHYDROUS CITRIC ACID; ASPARTAME; DOCUSATE SODIUM; MANNITOL; POVIDONE; SODIUM BENZOATE; SODIUM BICARBONATE

Drug Facts

Active ingredients

Aspirin 500 mg (NSAID*)
Caffeine 60 mg
*Nonsteroidal anti-inflammatory drug

Purpose

Aspirin…..Pain reliever
Caffeine…Alertness aid/Pain reliever aid

Uses

- for the temporary relief of minor aches and pains associated with a hangover
- helps restore mental alertness or wakefulness when experiencing fatigue or drowsiness associated with a hangover
- also for the temporary relief of headaches or body aches and pains alone

- for the temporary relief of headache pain
- also temporarily relieves minor aches and pains due to: backache muscle aches arthritis menstrual cramps hangover

- for the temporary relief of muscle aches and pain
- helps restore mental alertness when experiencing fatigue

Warnings

Reye’s syndrome: Children and teenagers who have or are recovering from chicken pox or flu-like symptoms should not use this product. When using this product. If changes in behavior with nausea and vomiting occur, consult a doctor because these symptoms could be an early sign of Reyes syndrome, a rare but serious illness.

Allergy alert: Aspirin may cause a severe allergic reaction which may include:

- hives
- facial swelling
- asthma (wheezing)
- shock

Stomach bleeding warning:
This product contains a nonsteroidal anti-inflammatory drug (NSAID) which may cause severe stomach bleeding. The chance is higher if you

- are age 60 or older
- have had stomach ulcers or bleeding problems
- take a blood thinning (anticoagulant) or steroid drug
- take other drugs containing prescription or non-prescription NSAIDs (aspirin, ibuprofen, naproxen, or others)
- have 3 or more alcoholic drinks every day while using this product
- take more or for a longer time than directed

Do not use

- if you have ever had an allergic reaction to aspirin or any other pain reliever/fever inducer

Ask a doctor before use if

- stomach bleeding warning applies to you
- you have a history of stomach problems, such as heartburn
- you have high blood pressure, heart disease, liver cirrhosis, or kidney disease
- you are taking a diuretic
- you have asthma
- you have a sodium-restricted diet

Ask a doctor or phamacist before use if you are

taking a prescription drug for

- diabetes
- gout
- arthritis

Caffeine warning

- the recommended dose of this product contains about as much caffeine as a cup of coffee. Limit the use of caffeine-containing medications, foods, or beverages because too much caffeine may cause nervousness, irritability, irritability, sleeplessness, and occasionally rapid heart beat.
- for occasional use only. Do not use for more than 2 days for a hangover unless directed by a doctor. Not intended for use as a substitute for sleep. If fatigue or drowsiness persists or continues to occur, consult a doctor.

Stop use and ask a doctor if

- an allergic reaction occurs. Seek medical help right away.
- you experience any of the following signs of stomach bleeding:
  - feel faint
  - vomit blood
  - have bloody or black stools
  - have stomach pain that does not get better
- pain lasts for more than 10 days or gets worse
- new symptoms occur
- redness or swelling is present
- ringing in the ears or a loss of hearing occurs

If pregnant or breastfeeding

ask a health professional before use. It is especially important not to use aspiring during the last 3 months of pregnancy unless definitely directed to do so by a doctor because it may cause problems in the unborn child or complications during delivery.

Keep out of reach of children

In case of overdose, get medical help or contact a Poison Control Center right away.

Directions

- upon waking, fully dissolve 2 tablets in 16 oz. of water and drink
- do not exceed recommended dosage

Adults and children 12 years and over (up to 60 years of age) | 2 tablets every 6 hours, as needed, or as directed by a doctor. Do not exceed 8 tablets in 24 hours
Adults 60 years and over | 2 tablets every 6 hours, as needed, or as directed by a doctor. Do not exceed 4 tablets in 24 hours
Children under 12 years | Do not use

Other information

- each tablet contains: sodium 406 mg
- phenylketonurics: contains phenylalanine 12.6 mg per tablet
- store at room temperature (59–86°F). Protect from excessive heat.

Inactive ingredients

acesulfame potassium, anhydrous citric acid, aspartame, docusate sodium, flavors, mannitol, povidone, sodium benzoate, sodium bicarbonate

Questions or Comments?

1-800-970-1793 (weekdays)

Blowfish for Hangovers

Alertness Aid - Caffeine

Pain Reliever - Aspirin (NSAID)
12 effervescent tablets

Lemon Flavor

Blowfish for Headaches

20 effervescent tablets

Lemon Flavor

Alertness Aid - Caffeine

Pain Reliever - Aspirin (NSAID)

Blowfish Sport

Caffeinated Pain Relief

20 effervescent tablets

Lemon Flavor

Alertness Aid - Caffeine

Pain Reliever - Aspirin (NSAID)